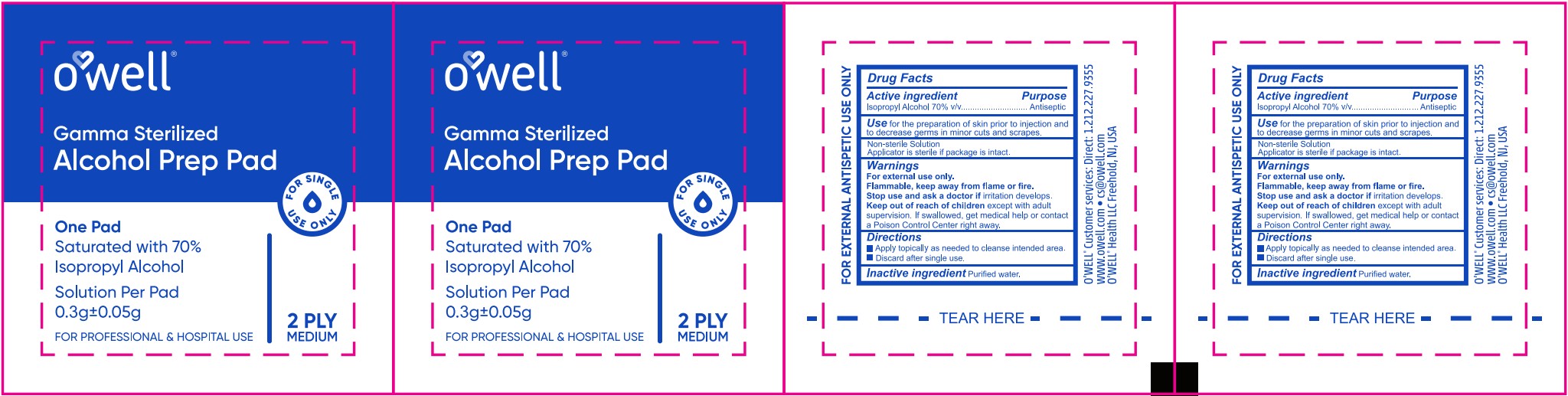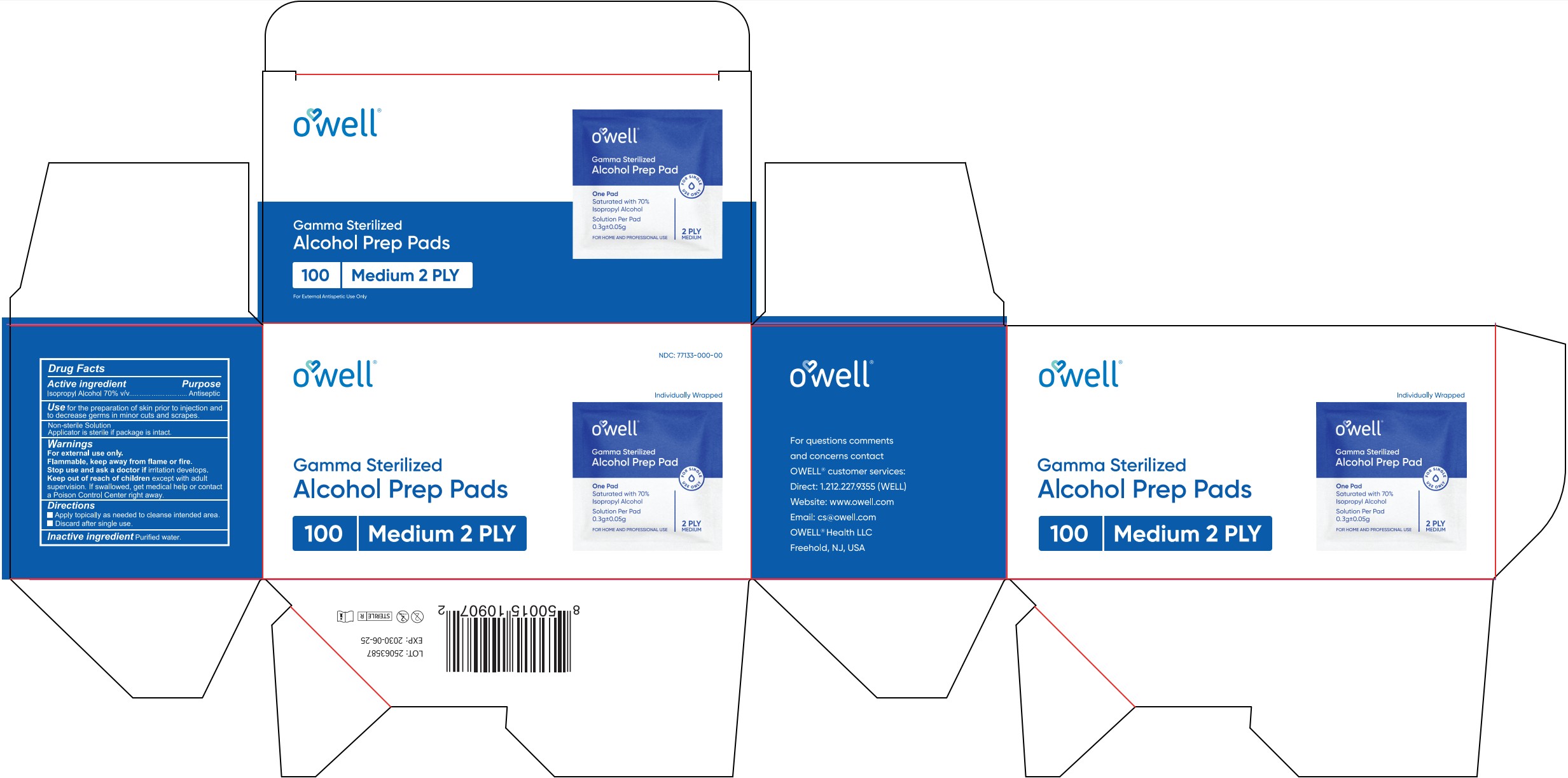 DRUG LABEL: Alcohol Prep Pad
NDC: 81849-005 | Form: CLOTH
Manufacturer: Shandong Lianfa Medical Plastic Products CO.,LTD
Category: otc | Type: HUMAN OTC DRUG LABEL
Date: 20251114

ACTIVE INGREDIENTS: ISOPROPYL ALCOHOL 70 mL/100 mL
INACTIVE INGREDIENTS: WATER

Pad, Isopropyl 70% v/v, 100pouch/box

Active ingredient

Isopropyl Alcohol, 70% v/v. Purpose: Antiseptic

Purpose

Antiseptic

Use

for the preparation of skin prior to injection and to decrease germs in minor cuts and scrapes.

Warnings

For external use only.

Flammable, keep away from flame or fire.

Stop use and ask a doctor if

irritation develops.

Keep out of reach of children

except with adult supervision. If swallowed, get medical help or contact a Poison Control Center right away.

Directions

- Apply topically as needed to cleanse intended area.
- Discard after single use.

Inactive ingredient

Purified water.